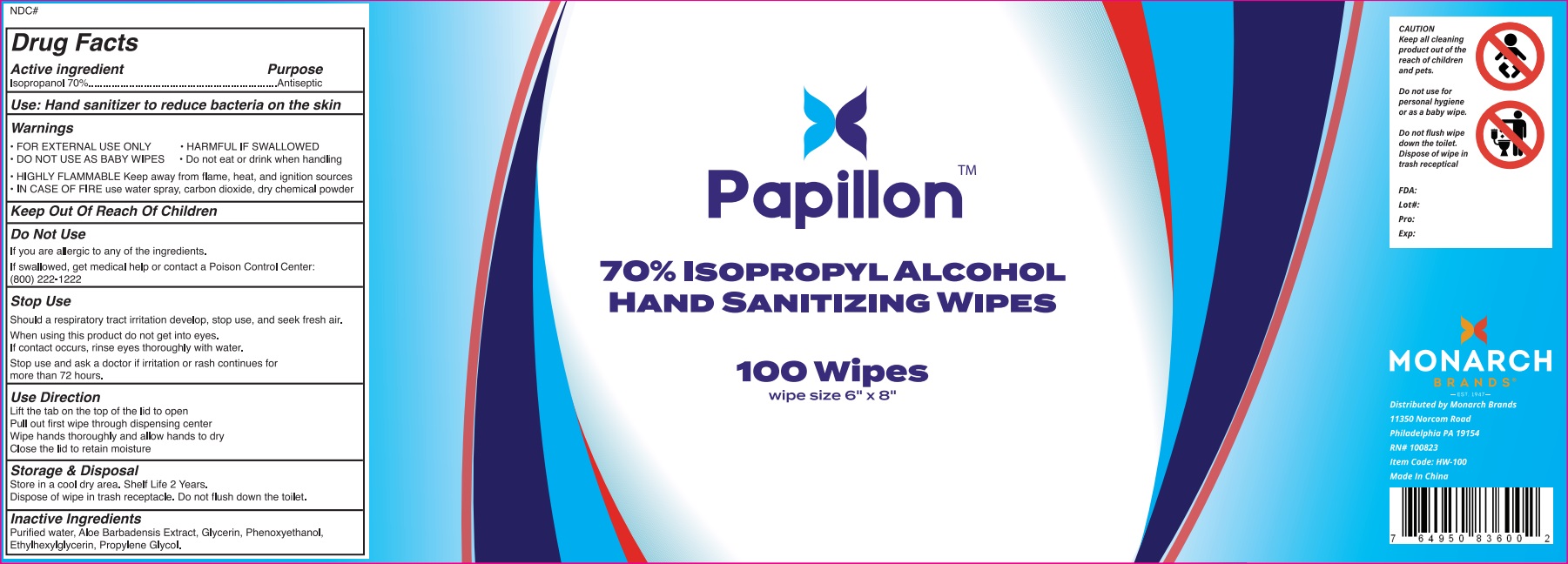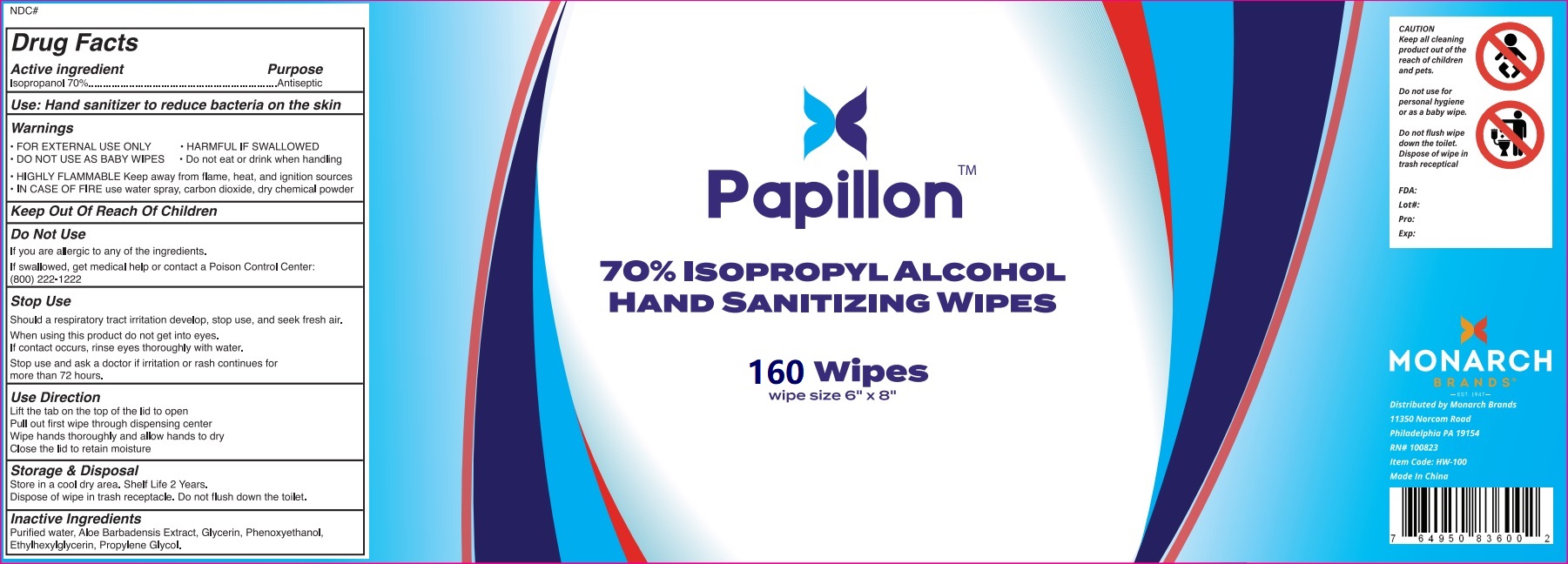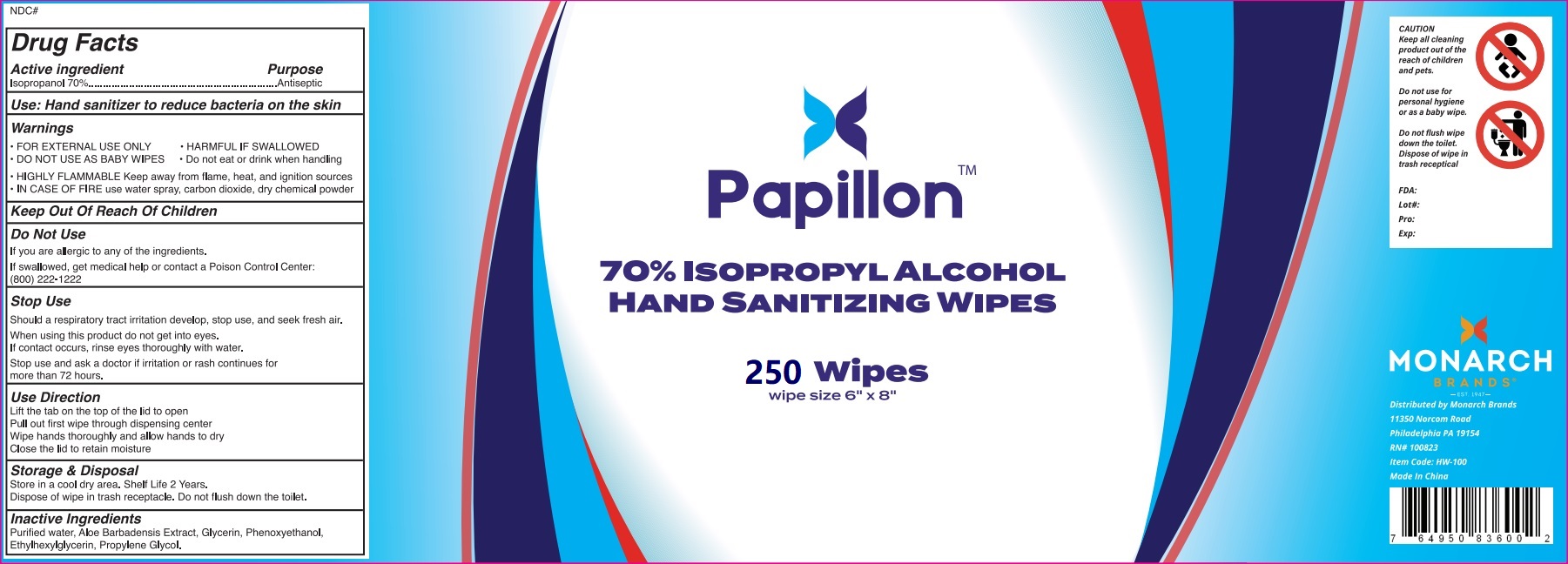 DRUG LABEL: Isopropanol Wipes
NDC: 81991-001 | Form: CLOTH
Manufacturer: Hangzhou Jiexiang Technology Co., Ltd.
Category: otc | Type: HUMAN OTC DRUG LABEL
Date: 20230301

ACTIVE INGREDIENTS: ISOPROPYL ALCOHOL 70 g/100 1
INACTIVE INGREDIENTS: GLYCERIN; ALOE VERA FLOWER; WATER; ETHYLHEXYLGLYCERIN; PROPYLENE GLYCOL; PHENOXYETHANOL

81991-001
Isopropanol Wipes

Active Ingredient(s)

Isopropanol 70%

Purpose

Antiseptic

Use

Hand sanitizer to reduce bacteria on the skin

Warnings

·FOR EXTERNAL USE ONLY

Do not use

If you are alergic to any of the ingredients.
If swallowed, get medical help or contact a Poison Control Center：(800)222-1222

DO NOT USE AS BABY WIPES

·HARMFUL IF SWALLOWED
·Do note at or drink when handing
·HIGHLY FLAMMABLE Keep away from flame, heat, and ignition sources
·IN CASE OF FIRE use water spray, carbon dioxide, dry chemical powder

When using this product do not get into eyes.
If contact occurs, rinse eyes thoroughly with water.

Stop use and ask a doctor if irritation or rash continues for more than 72 hours.

Stop Use
Should a respiratory tract irritation develop, stop use, and seek fresh air.

Stop use and ask a doctor if irritation or rash continues for more than 72 hours.

Keep Out Of Reach Of Children

Directions

Use Direction
Lift the tab on the top of the lid to open
Pullout first wipe through dispensing center
Wipe hands thoroughly and allow hands to dry
Close the lid to retain moisture

Other information

Storage&Disposal
Store in a cool dry area.Shelf Life 2 Years.
Dispose of wipe in trash receptacle.Do not flush down the toilet.

Inactive ingredients

Purified water, Aloe Barbadensis Extract, Glycerin, Phenoxyethanol, Ethylhexylglycerin, Propylene Glycol.

Package Label - Principal Display Panel

81991-001-01 100cloth